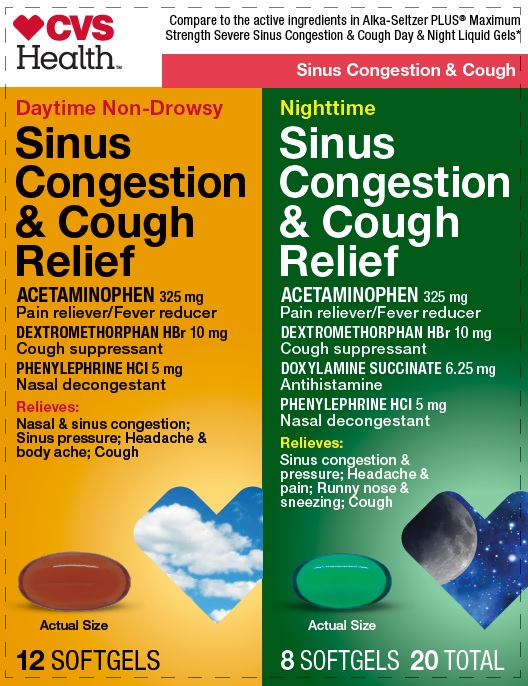 DRUG LABEL: Non Drowsy DAYTIME  and NIGHTTIME Sinus Congestion and Cough Relief
NDC: 69842-824 | Form: KIT | Route: ORAL
Manufacturer: CVS PHARMACY, INC.
Category: otc | Type: HUMAN OTC DRUG LABEL
Date: 20241218

ACTIVE INGREDIENTS: ACETAMINOPHEN 325 mg/1 1; DEXTROMETHORPHAN HYDROBROMIDE 10 mg/1 1; PHENYLEPHRINE HYDROCHLORIDE 5 mg/1 1; ACETAMINOPHEN 325 mg/1 1; DEXTROMETHORPHAN HYDROBROMIDE 10 mg/1 1; PHENYLEPHRINE HYDROCHLORIDE 5 mg/1 1; DOXYLAMINE SUCCINATE 6.25 mg/1 1
INACTIVE INGREDIENTS: FD&C RED NO. 40; FD&C YELLOW NO. 6; GELATIN; GLYCERIN; POLYETHYLENE GLYCOL 400; POVIDONE; PROPYLENE GLYCOL; WATER; SORBITOL; SORBITAN; TITANIUM DIOXIDE; SODIUM HYDROXIDE; D&C YELLOW NO. 10; FD&C BLUE NO. 1; GELATIN; GLYCERIN; POLYETHYLENE GLYCOL 400; POVIDONE; PROPYLENE GLYCOL; WATER; SORBITOL; SORBITAN; TITANIUM DIOXIDE

CVS Health Non Drowsy Daytime and Nighttime Sinus Congestion and Cough Relief

Non Drowsy DAYTIME Sinus Congestion and Cough Relief Active ingredients (in each softgel)

Acetaminophen 325 mg

Dextromethorphan hydrobromide 10 mg
Phenylephrine hydrochloride 5 mg

NIGHTTIME Sinus Congestion and Cough Relief Active ingredients (in each softgel)

Acetaminophen 325 mg
Dextromethorphan hydrobromide 10 mg
Doxylamine succinate 6.25 mg
Phenylephrine hydrochloride 5 mg

Purposes

Non Drowsy DAYTIME Sinus Congestion and Cough Relief

Pain reliever/fever reducer

Cough suppressant

Nasal decongestant

Purposes

Nighttime Sinus Congestion and Cough Relief

Pain reliever/fever reducer

Cough suppressant

Antihistamine

Nasal decongestant

Uses

Non Drowsy DAYTIME Sinus Congestion and Cough Relief

- temporarily relieves these symptoms due to a cold or flu:
  - minor aches and pains
  - headache
  - cough
  - sore throat
  - nasal and sinus congestion
- temporarily reduces fever

Uses

NIghttime Sinus Congestion and Cough Relief

- temporarily relieves these symptoms due to a cold or flu:
  - minor aches and pains
  - headache
  - nasal and sinus congestion
  - cough
  - sore throat
  - runny nose
  - sneezing
- temporarily reduces fever

Non Drowsy DAYTIME Sinus Congestion and Cough Relief Warnings

Liver warning

These products contain acetaminophen. Severe liver damage may occur if you take

- more than 4000 mg of Acetaminophen in 24 hours, which is the maximum daily amount for this product
- with other drugs containing acetaminophen
- 3 or more alcoholic drinks every day while using this product

Sore throat warning

If sore throat is severe, persists for more than 2 days, is accompanied or followed by fever, headache, rash, nausea, or vomiting, consult a doctor promptly.

Allergy alert: Acetaminophen may cause severe skin reactions. Symptoms may include:

- skin reddening
- blisters
- rash
  If a skin reaction occurs, stop use and seek medical help right away.

Do not use

- with any other drug containing acetaminophen (prescription or nonprescription). If you are not sure whether a drug contains acetaminophen, ask a doctor or pharmacist.
- if you are now taking a prescription monoamine oxidase inhibitor (MAOI) (certain drugs for depression, psychiatric, or emotional conditions, or Parkinson's disease), or for 2 weeks after stopping the MAOI drug. If you do not know if your prescription drug contains an MAOI, ask a doctor or pharmacist before taking this product.
- if you have ever had an allergic reaction to this product or any of its ingredients
- in children under 12 years of age

Ask a doctor before use if you have

- liver disease
- heart disease
- high blood pressure
- thyroid disease
- diabetes
- cough with excessive phlegm (mucus)
- difficulty in urination due to enlargement of the prostate gland
- persistent or chronic cough such as occurs with smoking, asthma, or emphysema

Ask a doctor or pharmacist before use if you are taking the blood thinning drug warfarin.

When using this product do not exceed recommended dosage

Stop use and ask a doctor if

- pain, cough, or nasal congestion gets worse or lasts more than 7 days
- fever gets worse or lasts more than 3 days
- redness or swelling is present
- new symptoms occur
- cough comes back or occurs with rash or headache that lasts.

These could be signs of a serious condition.

- nervousness, dizziness, or sleeplessness occurs

PREGNANCY OR BREAST FEEDING

If pregnant or breast-feeding, ask a health professional before use.

Keep out of reach of children.

In case of overdose, get medical help or contact a Poison Control Center right away. Quick medical attention is critical for adults as well as for children even if you do not notice any signs or symptoms.

Nighttime Sinus Congestion and Cough Relief Warnings

Liver warning

These products contain acetaminophen. Severe liver damage may occur if you take

- more than 4000 mg of Acetaminophen in 24 hours, which is the maximum daily amount for this product
- with other drugs containing acetaminophen
- 3 or more alcoholic drinks every day while using this product

Sore throat warning

If sore throat is severe, persists for more than 2 days, is accompanied or followed by fever, headache, rash, nausea, or vomiting, consult a doctor promptly.

Allergy alert: Acetaminophen may cause severe skin reactions. Symptoms may include:

- skin reddening
- blisters
- rash
  If a skin reaction occurs, stop use and seek medical help right away.

Do not use to sedate children.

Do not use

- with any other drug containing acetaminophen (prescription or nonprescription). If you are not sure whether a drug contains acetaminophen, ask a doctor or pharmacist.
- if you are now taking a prescription monoamine oxidase inhibitor (MAOI) (certain drugs for depression, psychiatric, or emotional conditions, or Parkinson's disease), or for 2 weeks after stopping the MAOI drug. If you do not know if your prescription drug contains an MAOI, ask a doctor or pharmacist before taking this product.
- if you have ever had an allergic reaction to this product or any of its ingredients
- in children under 12 years of age

Ask a doctor before use if you have

- liver disease
- heart disease
- high blood pressure
- thyroid disease
- diabetes
- glaucoma
- cough with excessive phlegm (mucus)
- a breathing problem such as emphysema or chronic bronchitis
- difficulty in urination due to enlargement of the prostate gland
- persistent or chronic cough such as occurs with smoking, asthma, or emphysema

Ask a doctor or pharmacist before use if you are

- taking the blood thinning drug warfarin
- taking sedatives or tranquilizers

When using this product

- do not exceed recommended dosage
- may cause marked drowsiness
- avoid alcoholic drinks
- alcohol, sedatives, and tranquilizers may increase drowsiness
- be careful when driving a motor vehicle or operating machinery
- excitability may occur, especially in children

Stop use and ask a doctor if

- pain, cough, or nasal congestion gets worse or lasts more than 7 days
- fever gets worse or lasts more than 3 days
- redness or swelling is present
- new symptoms occur
- cough comes back or occurs with rash or headache that lasts.

These could be signs of a serious condition.

- nervousness, dizziness, or sleeplessness occurs

PREGNANCY OR BREAST FEEDING

If pregnant or breast-feeding, ask a health professional before use.

Keep out of reach of children.

In case of overdose, get medical help or contact a Poison Control Center right away. Quick medical attention is critical for adults as well as for children even if you do not notice any signs or symptoms.

Non Drowsy DAYTIME Sinus Congestion and Cough Relief Directions

- do not take more than the recommended dose
- adults and children 12 years and over: take 2 softgels with water every 4 hours. Do not exceed 10 softgels in 24 hours or as directed by a doctor.
- children under 12 years: do not use

Nighttime Sinus Congestion and Cough Relief Directions

- do not take more than the recommended dose
- adults and children 12 years and over: take 2 softgels with water every 4 hours. Do not exceed 10 softgels in 24 hours or as directed by a doctor.
- children under 12 years: do not use

Non Drowsy DAYTIME Sinus Congestion and Cough Relief Other information

- store at room temperature. Avoid excessive heat.

Nighttime Sinus Congestion and Cough Relief Other information

- store at room temperature. Avoid excessive heat.

Non Drowsy DAYTIME Sinus Congestion and Cough Relief Inactive ingredients

FD&C Red# 40, FD&C Yellow# 6, gelatin, glycerin, polyethylene glycol,
povidone, propylene glycol, purified water, sorbitol sorbitan, titanium
dioxide

Nighttime Sinus Congestion and Cough Relief Inactive ingredients

D&C Yellow No. 10, FD&C Blue No. 1, gelatin, glycerin, polyethylene
glycol, povidone, propylene glycol, purified water, sorbitol sorbitan,
sodium hydroxide†, titanium dioxide
†may contain this ingredient

Non Drowsy DAYTIME Sinus Congestion and Cough Relief

Questions or comments?1-888-333-9792

Nighttime Sinus Congestion and Cough Relief

Questions or comments?1-888-333-9792